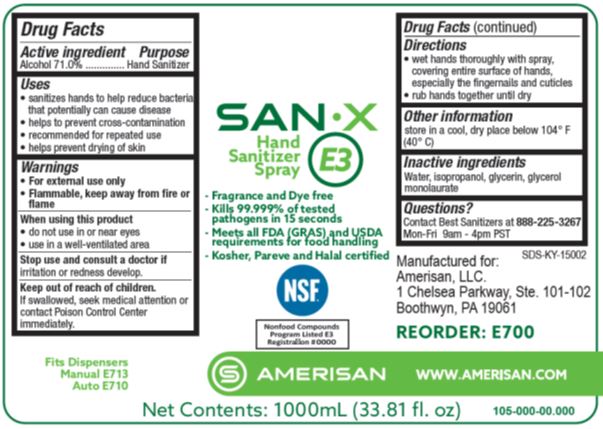 DRUG LABEL: SAN X E3
NDC: 69884-700 | Form: SPRAY
Manufacturer: Amerisan, LLC
Category: otc | Type: HUMAN OTC DRUG LABEL
Date: 20241216

ACTIVE INGREDIENTS: ALCOHOL 71 mL/100 mL
INACTIVE INGREDIENTS: ISOPROPYL ALCOHOL; WATER; GLYCERIN; GLYCERYL LAURATE

SAN X E3 69884-700

Active ingredient

Alcohol 71.0%

Purpose

Hand Sanitizer

Uses

- sanitizes hands to help reduce bacteria that potentially can cause disease
- helps to prevent cross-contamination
- recommended for repeated use
- helps prevent drying of the skin

Warnings

- For external use only
- Flammable, keep away from fire or flame

When using this product

- do not use in or near eyes
- use in a well-ventilated area

Stop use and consult a doctor ifirritation or redness develop.

Keep out of reach of children.

If swallowed, seek medical attention or contact Poison Control Center immediately.

Directions

- wet hands thoroughly with spray, covering entire surfaces of hands, especially the fingernails and cuticles
- rub hands together until dry

Other information

store in a cool, dry place below 104 F (40 C)

Inactive ingredients

Water, isopropanol, glycerin, glycerol monolaurate

Questions?

Contact Best Sanitizers at 888-225-3267Mon-Fri 9 am - 4 pm PST

PACKAGE LABEL

SAN X

E3

Hand

Sanitizer

Spray

- Fragrance and Dye free
- Kills 99.999% of tested

pathogens in 15 seconds

- Meets all FDA (GRAS) and USDA

requirements for food handling

- Kosher, Pareve and Halal certified

NSF

Nonfood Compounds

Program Listed E3

Registration #

AMERISAN

Net Contents: 1000mL (33.81 fl. oz)